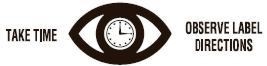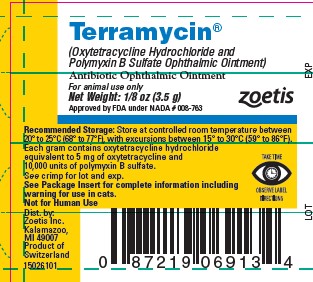 DRUG LABEL: Terramycin
NDC: 54771-1096 | Form: OINTMENT
Manufacturer: Zoetis Inc.
Category: animal | Type: PRESCRIPTION ANIMAL DRUG LABEL
Date: 20250924

ACTIVE INGREDIENTS: OXYTETRACYCLINE HYDROCHLORIDE 5 mg/1 g; POLYMYXIN B SULFATE 10000 [USP'U]/1 g

Terramycin®

Terramycin®
(Oxytetracycline Hydrochloride and Polymyxin B Sulfate Ophthalmic Ointment)
Antibiotic Ophthalmic Ointment

CAUTION

Federal law restricts this drug to use by or on the order of a licensed veterinarian.

DESCRIPTION

Terramycin (Oxytetracycline Hydrochloride and Polymyxin B Sulfate Ophthalmic Ointment) is an antibiotic, bright yellow in color, possessing potent antimicrobial activity. It is one of the most versatile of the broad-spectrum antibiotics, and is effective in the treatment of infections due to gram-positive and gram-negative bacteria, both aerobic and anaerobic, spirochetes, rickettsiae, and certain of the larger viruses.
Polymyxin B sulfate is one of a group of related antibiotics derived from Bacillus polymyxa. The polymyxins are rapidly bactericidal, this action being exclusively against gram-negative bacteria.
The broad-spectrum effectiveness of Terramycin against both gram-positive and gram-negative organisms is enhanced by the particular effectiveness of polymyxin B against infections associated with gram-negative organisms, especially those due to Pseudomonasaeruginosa, where polymyxin B is the antibiotic of choice. In addition, there is evidence to indicate that polymyxin B sulfate possesses some antifungal activity. The combined antibacterial effect of Terramycin plus polymyxin is at least additive and, in many instances, an actual synergistic action is obtained.
Terramycin is an ointment of oxytetracycline hydrochloride and polymyxin B sulfate in a special petrolatum base. Each gram of ointment contains oxytetracycline HCl equivalent to 5 mg of oxytetracycline and 10,000 units of polymyxin B as the sulfate.

INDICATIONS AND USAGE

Terramycin is indicated for the prophylaxis and local treatment of superficial ocular infections due to oxytetracycline and polymyxin-sensitive organisms, including infections due to streptococci, rickettsiae, E. coli, and A. aerogenes, such as conjunctivitis, keratitis, pink eye, corneal ulcer, blepharitis in dogs, cats, cattle, sheep, and horses; ocular infections due to secondary bacterial complications of distemper in dogs, and bacterial inflammatory conditions which may occur secondary to other infectious diseases in the above species.

WARNING

Serious, life threatening, hypersensitivity (anaphylactic) reactions have been reported in some cats following application of antibiotic ophthalmic preparations. If your cat has swelling of the face, itching, appears weak, vomits, or has difficulty breathing within 4 hours of application you should discontinue treatment and contact your veterinarian immediately.
Note: The use of oxytetracycline and other antibiotics may result in an overgrowth of resistant organisms such as Monilia, staphylococci, and other species of bacteria. If new infections due to nonsensitive bacteria or fungi appear during therapy, appropriate measures should be taken.

DOSAGE AND ADMINISTRATION

Terramycin (Oxytetracycline Hydrochloride and Polymyxin B Sulfate Ophthalmic Ointment) should be administered topically to the eye 2–4 times daily.

RECOMMENDED STORAGE

Store at controlled room temperature between 20° to 25°C (68° to 77°F), with excursions between 15° to 30°C (59° to 86°F).

HOW SUPPLIED

1/8-oz (3.5-g) tube

For Animal Use Only
Not for Human Use
Approved by FDA under NADA # 008-763
zoetis
Distributed by:
Zoetis Inc.
Kalamazoo, MI 49007

Revised: June 2022
23288603

PRINCIPAL DISPLAY PANEL - 3.5 g Tube Label

15026101